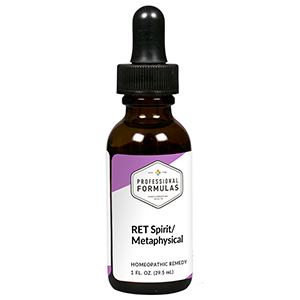 DRUG LABEL: RET Spirit/Metaphysical
NDC: 63083-7013 | Form: LIQUID
Manufacturer: Professional Complementary Health Formulas
Category: homeopathic | Type: HUMAN OTC DRUG LABEL
Date: 20190815

ACTIVE INGREDIENTS: CANIS LUPUS FAMILIARIS MILK 100 [hp_X]/29.5 mL; AGAVE ATROVIRENS TOP 100 [hp_X]/29.5 mL; ZIZIA AUREA WHOLE 200 [hp_X]/29.5 mL; SALIX ALBA FLOWERING TOP 3 [hp_X]/29.5 mL; ZANTEDESCHIA AETHIOPICA FLOWER 3 [hp_X]/29.5 mL
INACTIVE INGREDIENTS: ALCOHOL; WATER

RET13

ACTIVE INGREDIENTS

1 FL. OZ. contains
Lac caninum 100X (7.38 mL)
Agave tequilana 100C (7.38 mL)
Zizia aurea 200C (7.38 mL)
Willow flower essence 3X (3.68 mL)
Calla lily flower essence 3X (2.45 mL)
Wild rose flower essence 3X (1.23 mL)

QUESTIONS

Professional Formulas

PO Box 2034 Lake Oswego, OR 97035

INDICATIONS

Temporarily relieves contempt or disdain, apathy, lost motivation or ambition, self-pity, resentment, bitterness, despondency, sadness, indifference, or anxiousness.*

PURPOSE

*Claims based on traditional homeopathic practice, not accepted medical evidence. Not FDA evaluated.

WARNINGS

In case of overdose, get medical help or contact a poison control center right away.

Keep out of the reach of children.

PREGNANCY OR BREAST FEEDING

If pregnant or breastfeeding, ask a healthcare professional before use.

DIRECTIONS

Place drops under tongue 30 minutes before/after meals. Adults and children 12 years and over: Take 5 drops up to 4 times per day for up to one month. Consult a physician for use in children under 12 years of age.

OTHER INFORMATION

Tamper resistant. If seal is broken, do not use. After opening, close container tightly and store at room temperature away from heat.

INACTIVE INGREDIENTS

20% ethanol, purified water.

LABEL

Est 1985

Professional Formulas

Complementary Health

RET Spirit/Metaphysical

Homeopathic Remedy

1 FL. OZ. (29.5 mL)